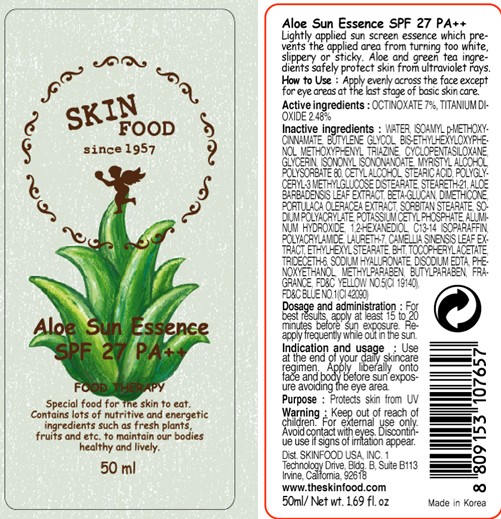 DRUG LABEL: ALOE SUN ESSENCE
NDC: 76214-030 | Form: CREAM
Manufacturer: SKINFOOD CO., LTD.
Category: otc | Type: HUMAN OTC DRUG LABEL
Date: 20110929

ACTIVE INGREDIENTS: OCTINOXATE 3.5 mL/50 mL; TITANIUM DIOXIDE 1.24 mL/50 mL
INACTIVE INGREDIENTS: WATER; BUTYLENE GLYCOL; CYCLOMETHICONE 5; GLYCERIN; ISONONYL ISONONANOATE; MYRISTYL ALCOHOL; POLYSORBATE 80; CETYL ALCOHOL; STEARIC ACID; STEARETH-21; ALOE VERA LEAF; DIMETHICONE; PURSLANE; SORBITAN MONOSTEARATE; PHENOXYETHANOL; POTASSIUM CETYL PHOSPHATE; ALUMINUM HYDROXIDE; METHYLPARABEN; 1,2-HEXANEDIOL; C13-14 ISOPARAFFIN; LAURETH-7; BUTYLPARABEN; GREEN TEA LEAF; ETHYLHEXYL STEARATE; BUTYLATED HYDROXYTOLUENE; TRIDECETH-6; HYALURONATE SODIUM; EDETATE DISODIUM

Drug Facts

Active ingredients: OCTINOXATE 7%, TITANIUM DIOXIDE 2.48%

Inactive ingredients:
WATER, ISOAMYL p-METHOXYCINNAMATE, BUTYLENE GLYCOL, BIS-ETHYLHEXYLOXYPHENOL METHOXYPHENYL TRIAZINE, CYCLOPENTASILOXANE, GLYCERIN, ISONONYL ISONONANOATE, MYRISTYL ALCOHOL, POLYSORBATE 80, CETYL ALCOHOL, STEARIC ACID, POLYGLYCERYL-3 METHYLGLUCOSE DISTEARATE, STEARETH-21, ALOE BARBADENSIS LEAF EXTRACT, BETA-GLUCAN, DIMETHICONE, PORTULACA OLERACEA EXTRACT, SORBITAN STEARATE, SODIUM POLYACRYLATE, POTASSIUM CETYL PHOSPHATE, ALUMINUM HYDROXIDE, 1,2-HEXANEDIOL, C13-14 ISOPARAFFIN, POLYACRYLAMIDE, LAURETH-7, CAMELLIA SINENSIS LEAF EXTRACT, ETHYLHEXYL STEARATE, BHT, TOCOPHERYL ACETATE, TRIDECETH-6, SODIUM HYALURONATE, DISODIUM EDTA, PHENOXYETHANOL, METHYLPARABEN, BUTYLPARABEN, FRAGRANCE

Purpose: Protects skin from UV rays.

Warnings:
For external use only.
Avoid contact with eyes.
Discontinue use if signs of irritation appear.

Keep out of reach of children:
Keep out of reach of children.

Indication and usage:
Use at the end of your daily skincare regimen.
Apply liberally onto face and body before sun exposure avoiding the eye area.

Dosage and administration:
For best results, apply at least 15 to 20 minutes before sun exposure.
Reapply frequently while out in the sun.